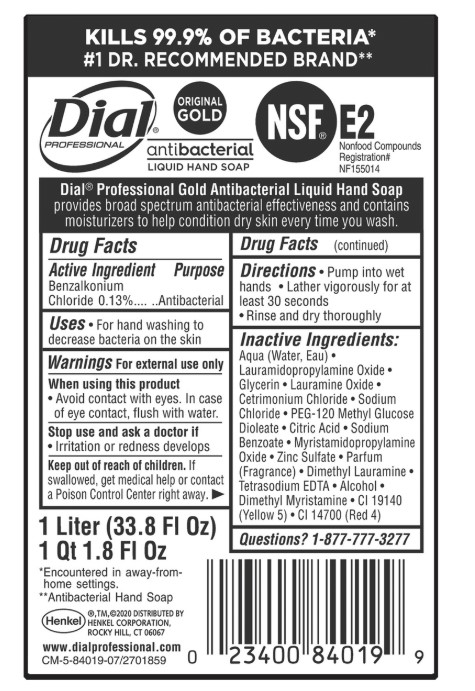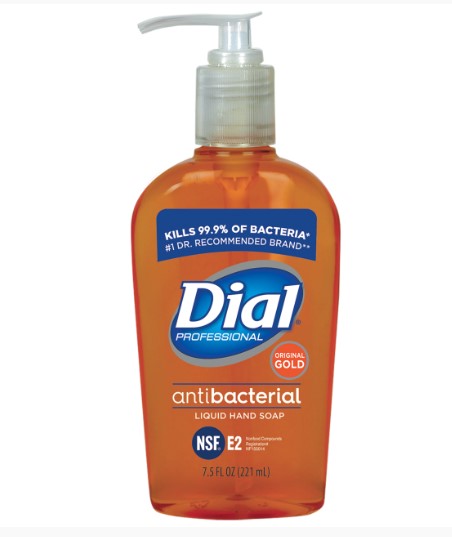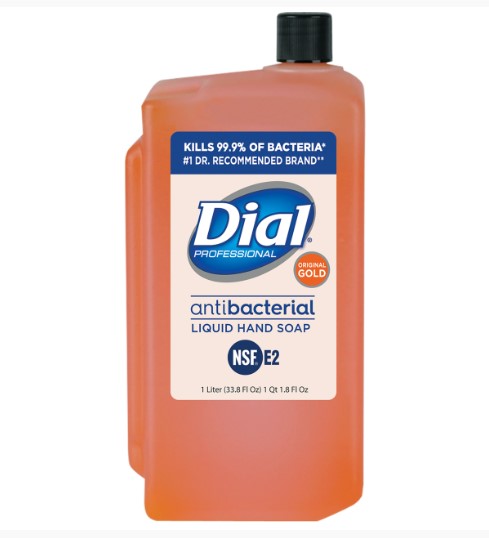 DRUG LABEL: Dial Professional Original Gold Antibacterial
NDC: 54340-135 | Form: LIQUID
Manufacturer: Henkel Corporation
Category: otc | Type: HUMAN OTC DRUG LABEL
Date: 20251216

ACTIVE INGREDIENTS: BENZALKONIUM CHLORIDE 0.13 g/100 mL
INACTIVE INGREDIENTS: WATER 90.54 mL/100 mL

Dial Professional Original Gold Antibacterial Liquid Hand Soap
Dial Professional Gold Antibacterial Liquid Hand Soap 144/2oz
Dial Professional Gold Antibacterial Liquid Hand Soap - 12/7.5oz Decor Pump
Dial Professional Gold Antibacterial Liquid Hand Soap - 12/16oz Pump
Dial Professional Gold Antibacterial Liquid Hand Soap 8/1L Refill
Dial Professional Gold Antibacterial Liquid Hand Soap - Refill 4/1Gallon
Versa™ (Formerly Eco-Smart) Dial Professional Liquid Hand Soap Gold - Refill 6/15 oz

Dial® Professional Original Gold Antibacterial Liquid Hand Soap

Aqua (Water, Eau)
Lauramidopropylamine Oxide
Glycerin
Cetrimonium Chloride
Lauramine Oxide
Sodium Chloride
PEG-120 Methyl Glucose Dioleate
Citric Acid
Sodium Benzoate
Myristamidopropylamine Oxide
Zinc Sulfate
Parfum (Fragrance)
Dimethyl Lauramine
Tetrasodium EDTA
Hydrogen Peroxide
Alcohol
Dimethyl Myristamine
CI 19140 (Yellow 5)

CI 14700 (Red 4)

Warnings

Warnings For external use only

When using this product•Avoid contact with eyes •

Stop use and ask a doctor if•Irritation or redness develops OR Stop use and ask a doctor ifirritation or redness develops
Keep out of reach of children. •If swallowed, get medical help or contact a Poison Control Center right away

Uses

For hand washing to decrease bacteria on the skin

Dial Professional Original Gold Antibacterial Liquid Hand Soap

Benzalkonium Chloride